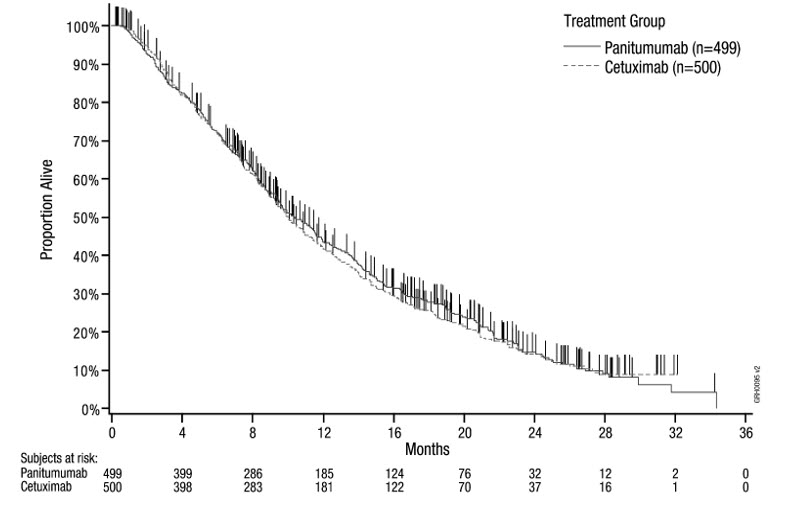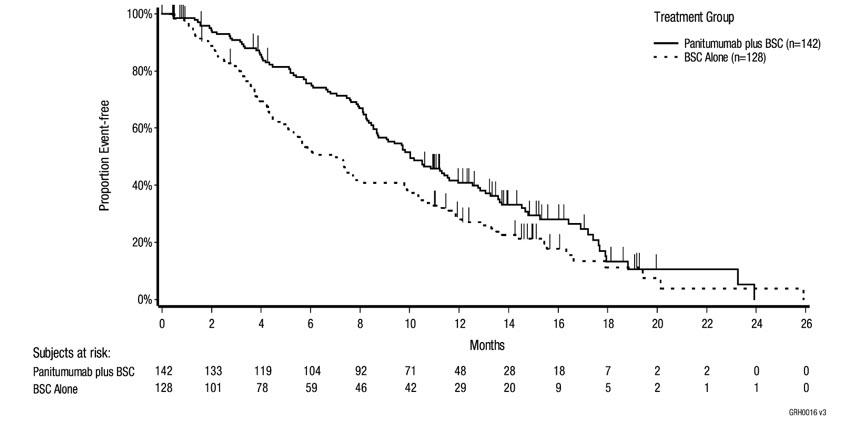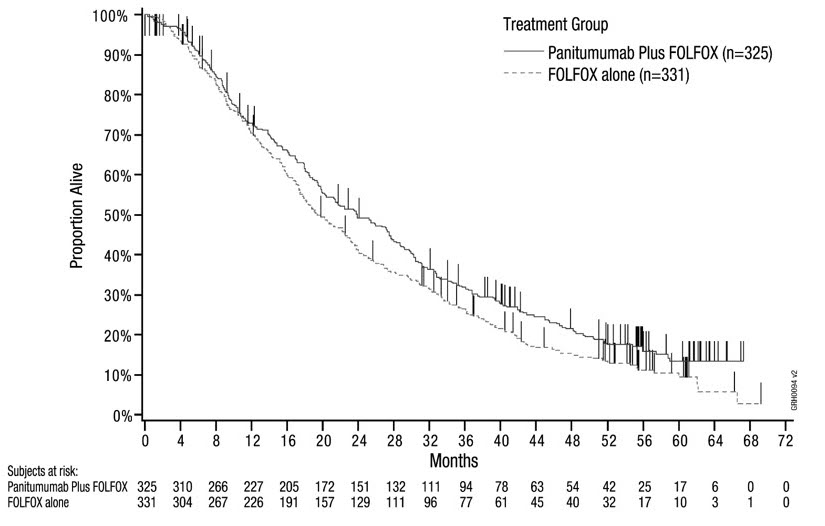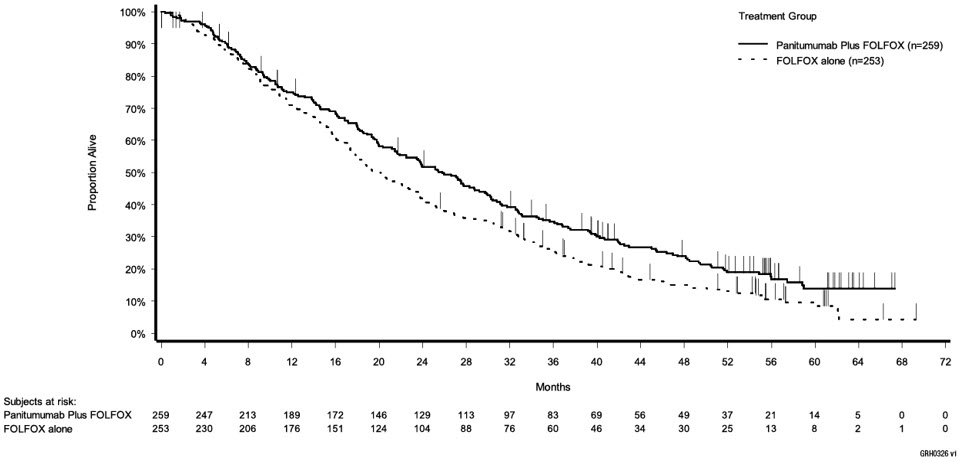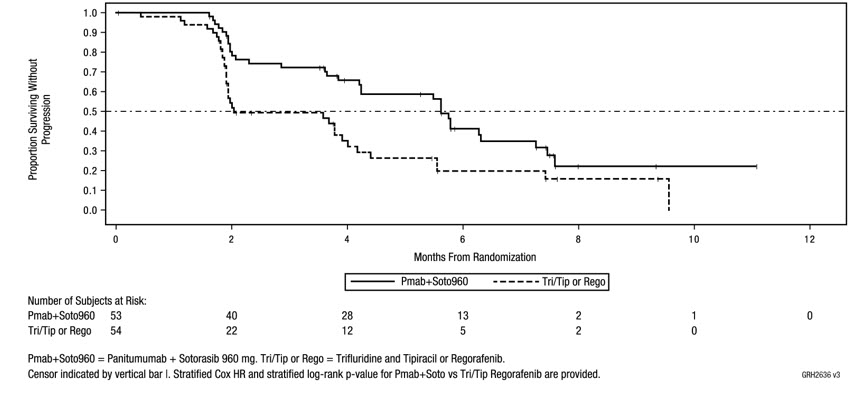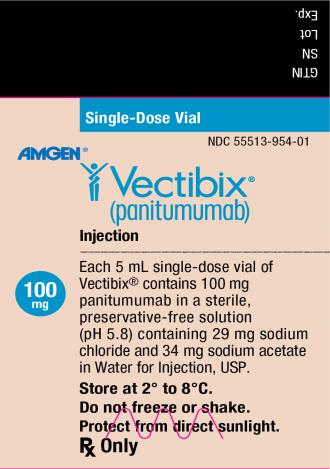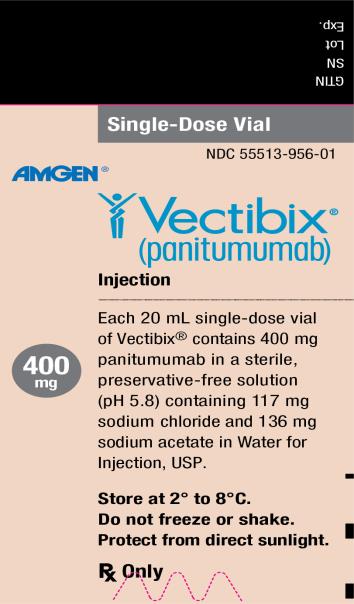 DRUG LABEL: Vectibix
NDC: 55513-954 | Form: SOLUTION
Manufacturer: Amgen Inc
Category: prescription | Type: HUMAN PRESCRIPTION DRUG LABEL
Date: 20250603

ACTIVE INGREDIENTS: PANITUMUMAB 100 mg/5 mL
INACTIVE INGREDIENTS: SODIUM ACETATE 34 mg/5 mL; SODIUM CHLORIDE 29 mg/5 mL; WATER

HIGHLIGHTS OF PRESCRIBING INFORMATION

These highlights do not include all the information needed to use VECTIBIX safely and effectively. See full prescribing information for VECTIBIX.
VECTIBIX® (panitumumab) Injection for intravenous use
Initial U.S. Approval: 2006

WARNING: DERMATOLOGIC TOXICITY

See full prescribing information for complete boxed warning.

- Dermatologic toxicities were reported in 90% of patients and were severe in 15% of patients receiving monotherapy. (2.3, 5.1, 6.1)

RECENT MAJOR CHANGES

- Indications and Usage (1) | 01/2025
- Dosage and Administration (2.1, 2.2, 2.3) | 01/2025
- Warnings and Precautions (5.1, 5.2, 5.3, 5.5, 5.6, 5.8) | 01/2025

1 INDICATIONS AND USAGE

Vectibix is an epidermal growth factor receptor (EGFR) antagonist indicated for the treatment of:

Adult patients with wild-type RAS (defined as wild-type in both KRAS and NRAS as determined by an FDA-approved test) Metastatic Colorectal Cancer (mCRC)*:

- In combination with FOLFOX for first-line treatment. (1, 14.2)
- As monotherapy following disease progression after prior treatment with fluoropyrimidine, oxaliplatin, and irinotecan-containing chemotherapy. (1, 14.1)

KRAS G12C-mutated Metastatic Colorectal Cancer (mCRC)*

- In combination with sotorasib, for the treatment of adult patients with KRAS G12C-mutated mCRC, as determined by an FDA-approved test, who have received prior treatment with fluoropyrimidine-, oxaliplatin-, and irinotecan-based chemotherapy. (1)

*Limitations of Use: Vectibix is not indicated for the treatment of patients with RAS-mutant mCRC unless used in combination with sotorasib in KRAS G12C-mutated mCRC. Vectibix is not indicated for the treatment of patients with mCRC for whom RAS mutation status is unknown (1, 2.1, 5.2, 12.1, 14.3).

2 DOSAGE AND ADMINISTRATION

- RAS Wild-Type mCRC: Administer 6 mg/kg every 14 days as an intravenous infusion over 60 minutes (≤ 1000 mg) or 90 minutes (> 1000 mg). (2)
- KRAS G12C-mutated mCRC: Administer 6 mg/kg every 14 days as an intravenous infusion over 60 minutes (≤ 1000 mg) or 90 minutes (> 1000 mg) in combination with sotorasib. (2)

3 DOSAGE FORMS AND STRENGTHS

Injection: 100 mg/5 mL (20 mg/mL) and 400 mg/20 mL (20 mg/mL) in single-dose vials. (3)

4 CONTRAINDICATIONS

None

5 WARNINGS AND PRECAUTIONS

- Dermatologic and Soft Tissue Toxicity: Monitor for dermatologic and soft tissue toxicities. Reduce dose for recurrent Grade 3 toxicity and withhold or discontinue Vectibix for severe or life-threatening complications. Limit sun exposure. (2.3, 5.1, 5.7)
- Increased tumor progression, increased mortality, or lack of benefit in patients with RAS-mutant mCRC, receiving Vectibix monotherapy or in combination with oxaliplatin-based chemotherapy. (2.1, 5.2)
- Electrolyte Depletion/Monitoring: Monitor electrolytes and institute appropriate treatment. (5.3)
- Infusion Reactions: Reduce infusion rate by 50% for mild to moderate reactions; terminate the infusion for severe infusion reactions. (2.3, 5.4)
- Pulmonary Fibrosis/Interstitial Lung Disease (ILD): Permanently discontinue Vectibix in patients developing ILD. (5.6)
- Ocular Toxicities: Monitor for keratitis, ulcerative keratitis, or corneal perforation. Interrupt or discontinue Vectibix for acute or worsening keratitis, ulcerative keratitis, or corneal perforation. (5.8)
- Embryo-fetal Toxicity: Can cause fetal harm. Advise females of reproductive potential of the potential risk to the fetus and to use effective contraception during treatment with Vectibix and for 2 months after the last dose. (5.10, 8.1, 8.3)

6 ADVERSE REACTIONS

- Most common adverse reactions (≥ 20%) of Vectibix as monotherapy are skin rash with variable presentations, paronychia, fatigue, nausea, and diarrhea. (6.1)
- Most common adverse reactions (≥ 20%) in clinical trials of Vectibix in combination with FOLFOX chemotherapy are diarrhea, stomatitis, mucosal inflammation, asthenia, paronychia, anorexia, hypomagnesemia, hypokalemia, rash, acneiform dermatitis, pruritus, and dry skin. (6.1)
- Most common adverse reactions (≥ 20%) in clinical trials of Vectibix in combination with sotorasib are rash, dry skin, diarrhea, stomatitis, fatigue and musculoskeletal pain. The most common Grade 3 or 4 laboratory abnormalities in ≥ 2 patients (4.3%) were decreased magnesium, decreased potassium, decreased corrected calcium, and increased potassium. (6.1)

To report SUSPECTED ADVERSE REACTIONS, contact Amgen Inc. at 1-800-77-AMGEN (1-800-772-6436) or FDA at 1-800-FDA-1088 or www.fda.gov/medwatch.

8 USE IN SPECIFIC POPULATIONS

- Lactation: Advise women not to breastfeed. (8.2)

FULL PRESCRIBING INFORMATION

WARNING: DERMATOLOGIC TOXICITY

Dermatologic Toxicity: Dermatologic toxicities occurred in 90% of patients and were severe (NCI-CTC Grade 3 and higher) in 15% of patients receiving Vectibix monotherapy [see Dosage and Administration (2.3), Warnings and Precautions (5.1) and Adverse Reactions (6.1)].

1 INDICATIONS AND USAGE

Metastatic Colorectal Cancer (mCRC)

- RAS Wild-Type mCRC
  Vectibix is indicated for the treatment of adult patients with wild-type RAS (defined as wild-type in both KRAS and NRAS as determined by an FDA-approved test) metastatic colorectal cancer (mCRC) [see Dosage and Administration (2.1)]:
  - As first-line therapy in combination with FOLFOX [see Clinical Studies (14.2)].
  - As monotherapy following disease progression after prior treatment with fluoropyrimidine-, oxaliplatin-, and irinotecan-containing chemotherapy [see Clinical Studies (14.1)].
- KRAS G12C-mutated mCRC
  Vectibix, in combination with sotorasib, is indicated for the treatment of adult patients with KRAS G12C-mutated mCRC, as determined by an FDA-approved test, who have received prior treatment with fluoropyrimidine-, oxaliplatin-, and irinotecan-based chemotherapy [see Dosage and Administration (2.1) and Clinical Studies (14.4)].

Limitations of Use: Vectibix is not indicated for the treatment of patients with RAS-mutant mCRC unless used in combination with sotorasib in KRAS G12C-mutated mCRC. Vectibix is not indicated for the treatment of patients with mCRC for whom RAS mutation status is unknown [see Dosage and Administration (2.1), Warnings and Precautions (5.2), Clinical Pharmacology (12.1) and Clinical Studies (14.3)].

2 DOSAGE AND ADMINISTRATION

2.1 Patient Selection

RAS Wild-Type mCRC

Prior to initiation of treatment with Vectibix as monotherapy, assess RAS mutational status in colorectal tumors and confirm the absence of a RAS mutation in exon 2 (codons 12 and 13), exon 3 (codons 59 and 61), and exon 4 (codons 117 and 146) of both KRAS and NRAS.

KRAS G12C-mutated mCRC

Prior to initiation of treatment with Vectibix in combination with sotorasib, confirm the presence of the KRAS G12C mutation using an FDA-approved test.

Information on FDA-approved tests for the detection of RAS mutations in patients with mCRC is available at: http://www.fda.gov/CompanionDiagnostics.

2.2 Recommended Dosage

RAS Wild-Type mCRC

The recommended dosage of Vectibix is 6 mg/kg, administered as an intravenous infusion every 14 days until disease progression or unacceptable toxicity [see Dosage and Administration (2.4)].

Appropriate medical resources for the treatment of severe infusion reactions should be available during Vectibix infusions [see Warnings and Precautions (5.4)].

KRAS G12C-mutated mCRC

Administer the first sotorasib dose prior to the first Vectibix infusion.

The recommended dosage for Vectibix in combination with sotorasib is 6 mg/kg, administered as an intravenous infusion every 14 days until disease progression, unacceptable toxicity, or until sotorasib is withheld or discontinued [see Dosage and Administration (2.3, 2.4)]. Refer to the sotorasib full prescribing information for recommended sotorasib dosing information.

Appropriate medical resources for the treatment of severe infusion reactions should be available during Vectibix infusions [see Warnings and Precautions (5.4)].

2.3 Dose Modifications

Dose Modifications for Vectibix in Combination with Sotorasib

When Vectibix is administered in combination with sotorasib, if treatment with sotorasib is temporarily withheld or permanently discontinued, temporarily withhold or permanently discontinue Vectibix, respectively [see Clinical Studies (14.4)].

Refer to the sotorasib full prescribing information for dose modifications for adverse reactions associated with the use of sotorasib.

Dose Modifications for Specific Adverse Reactions Associated with the Use of Vectibix

Infusion Reactions [see Warnings and Precautions (5.4) and Adverse Reactions (6.1, 6.2)]

- Reduce infusion rate by 50% in patients experiencing a mild or moderate (Grade 1 or 2) infusion reaction for the duration of that infusion.
- Terminate the infusion in patients experiencing severe infusion reactions. Depending on the severity and/or persistence of the reaction, permanently discontinue Vectibix.

Dermatologic Toxicity [see Boxed Warning, Warnings and Precautions (5.1) and Adverse Reactions (6.1, 6.2)]

- Upon first occurrence of a Grade 3 (NCI-CTC/CTCAE) dermatologic reaction, withhold 1 to 2 doses of Vectibix. If the reaction improves to < Grade 3, reinitiate Vectibix at the original dose.
- Upon the second occurrence of a Grade 3 (NCI-CTC/CTCAE) dermatologic reaction, withhold 1 to 2 doses of Vectibix. If the reaction improves to < Grade 3, reinitiate Vectibix at 80% of the original dose.
- Upon the third occurrence of a Grade 3 (NCI-CTC/CTCAE) dermatologic reaction, withhold 1 to 2 doses of Vectibix. If the reaction improves to < Grade 3, reinitiate Vectibix at 60% of the original dose.
- Upon the fourth occurrence of a Grade 3 (NCI-CTC/CTCAE) dermatologic reaction, permanently discontinue Vectibix.

Permanently discontinue Vectibix following the occurrence of a Grade 4 dermatologic reaction or for a Grade 3 (NCI-CTC/CTCAE) dermatologic reaction that does not recover after withholding 1 or 2 doses.

2.4 Preparation and Administration

For intravenous infusion only. Do not administer Vectibix as an intravenous push or bolus.

Preparation

Visually inspect parenteral drug products for particulate matter and discoloration prior to administration. Vectibix solution is colorless and may contain a small amount of visible translucent-to-white, amorphous, proteinaceous particles. Do not use if the solution is discolored or cloudy, or if foreign matter is present.

Prepare the solution for infusion, using aseptic technique, as follows:

- Do not shake the vial.
- Use a 21-gauge or larger gauge (smaller bore) hypodermic needle to withdraw the necessary amount of Vectibix for a dose of 6 mg/kg. Do not use needle-free devices (e.g., vial adapters) to withdraw vial contents.
- Dilute to a total volume of 100 mL with 0.9% sodium chloride injection, USP. Doses higher than 1000 mg should be diluted to 150 mL with 0.9% sodium chloride injection, USP. Do not exceed a final concentration of 10 mg/mL.
- Mix diluted solution by gentle inversion.
- Discard any unused portion of the vial.

Administration

- Administer using a low-protein-binding 0.2 µm or 0.22 µm in-line filter.
- Vectibix must be administered via infusion pump.
  - Flush line before and after Vectibix administration with 0.9% sodium chloride injection, USP, to avoid mixing with other drug products or intravenous solutions. Do not mix Vectibix with, or administer as an infusion with, other medicinal products. Do not add other medications to solutions containing panitumumab.
  - Infuse doses of 1000 mg or lower over 60 minutes through a peripheral intravenous line or indwelling intravenous catheter. If the first infusion is tolerated, administer subsequent infusions over 30 to 60 minutes. Administer doses higher than 1000 mg over 90 minutes.
- Use the diluted infusion solution of Vectibix within 6 hours of preparation if stored at room temperature, or within 24 hours of dilution if stored at 2° to 8°C (36° to 46°F). DO NOT FREEZE.

3 DOSAGE FORMS AND STRENGTHS

Injection: 100 mg/5 mL (20 mg/mL) colorless solution in single-dose vial.

Injection: 400 mg/20 mL (20 mg/mL) colorless solution in single-dose vial.

4 CONTRAINDICATIONS

None.

5 WARNINGS AND PRECAUTIONS

5.1 Dermatologic and Soft Tissue Toxicity

Vectibix can cause dermatologic toxicity, which may be severe. Clinical manifestations included, but were not limited to, acneiform dermatitis, pruritis, erythema, rash, skin exfoliation, paronychia, dry skin, and skin fissures.

Among 229 patients who received Vectibix as monotherapy, dermatologic toxicity occurred in 90% including Grade 3 (15%). Among 585 patients who received Vectibix in combination with FOLFOX, dermatologic toxicity occurred in 96% including Grade 4 (1%) and Grade 3 (32%). In 126 patients receiving Vectibix in combination with sotorasib across clinical studies, dermatologic toxicities occurred in 94%, including Grade 3 (16%) of patients.

Monitor patients who develop dermatologic or soft tissue toxicities while receiving Vectibix for the development of inflammatory or infectious sequelae. Life-threatening and fatal infectious complications including necrotizing fasciitis, abscesses, and sepsis have been observed in patients treated with Vectibix. Life-threatening and fatal bullous mucocutaneous disease with blisters, erosions, and skin sloughing has also been observed in patients treated with Vectibix. It could not be determined whether these mucocutaneous adverse reactions were directly related to EGFR inhibition or to idiosyncratic immune-related effects (e.g., Stevens-Johnson syndrome or toxic epidermal necrolysis). Withhold or discontinue Vectibix for dermatologic or soft tissue toxicity associated with severe or life-threatening inflammatory or infectious complications [see Boxed Warning and Adverse Reactions (6.1, 6.2)]. Dose modifications for Vectibix concerning dermatologic toxicity are provided [see Dosage and Administration (2.3)].

5.2 Increased Tumor Progression, Increased Mortality, or Lack of Benefit in Patients with RAS-Mutant mCRC Receiving Vectibix Monotherapy or in Combination with Oxaliplatin-based Chemotherapy

Vectibix monotherapy or in combination with oxaliplatin-based chemotherapy is not indicated for the treatment of patients with colorectal cancer that harbor somatic RAS mutations in exon 2 (codons 12 and 13), exon 3 (codons 59 and 61), and exon 4 (codons 117 and 146) of either KRAS or NRAS and hereafter is referred to as "RAS" [see Indications and Usage (1), Dosage and Administration (2.1), Clinical Pharmacology (12.1) and Clinical Studies (14.3)].

Retrospective subset analyses across several randomized clinical trials were conducted to investigate the role of RAS mutations on the clinical effects of anti-EGFR-directed monoclonal antibodies (panitumumab or cetuximab). Anti-EGFR antibodies in patients with tumors containing RAS mutations resulted in exposing those patients to anti-EGFR related adverse reactions without clinical benefit from these agents [see Indications and Usage (1) and Clinical Pharmacology (12.1)].

Additionally, in Study 20050203, 272 patients with RAS-mutant mCRC tumors received Vectibix in combination with FOLFOX and 276 patients received FOLFOX alone. In an exploratory subgroup analysis, overall survival (OS) was shorter (HR = 1.21, 95% CI: 1.01-1.45) in patients with RAS-mutant mCRC who received Vectibix and FOLFOX versus FOLFOX alone [see Indications and Usage (1)].

5.3 Electrolyte Depletion/Monitoring

Vectibix can cause progressively decreasing serum magnesium levels leading to severe (Grade 3 or 4) hypomagnesemia.

Among 229 patients who received Vectibix as monotherapy, decreased magnesium occurred in 38% including Grade 4 (1.3%) and Grade 3 (2.6%). Among 585 patients who received Vectibix in combination with FOLFOX, decreased magnesium occurred in 51% including Grade 4 (5%) and Grade 3 (6%). In 126 patients receiving Vectibix in combination with sotorasib across clinical studies, decreased magnesium occurred in 69%, including Grade 4 (2.4%) and Grade 3 (14%).

Monitor patients for hypomagnesemia and hypocalcemia prior to initiating Vectibix treatment, periodically during Vectibix treatment, and for up to 8 weeks after the completion of treatment. Other electrolyte disturbances, including hypokalemia, have also been observed. Replete magnesium and other electrolytes as appropriate.

5.4 Infusion Reactions

In Study 20020408, 4% of patients experienced infusion reactions and 1% of patients experienced severe infusion reactions (NCI-CTC Grade 3-4).

Infusion reactions, manifesting as fever, chills, dyspnea, bronchospasm, and hypotension, can occur following Vectibix administration [see Adverse Reactions (6.1, 6.2)]. Fatal infusion reactions occurred in postmarketing experience. Terminate the infusion for severe infusion reactions [see Dosage and Administration (2.3)].

5.5 Acute Renal Failure

Severe diarrhea and dehydration, leading to acute renal failure and other complications, have been observed in patients treated with Vectibix.

Among 229 patients who received Vectibix as monotherapy, acute renal failure occurred in 2% including Grade 3 or 4 (2%). Among 585 patients who received Vectibix in combination with FOLFOX, acute renal failure occurred in 2% including Grade 3 or 4 (2%). In 126 patients receiving Vectibix in combination with sotorasib across clinical studies, acute renal failure occurred in 3.2% including Grade 3 (0.8%).

Monitor patients for diarrhea and dehydration, provide supportive care (including anti-emetic or anti-diarrheal therapy) as needed, and withhold Vectibix if necessary.

5.6 Pulmonary Fibrosis/Interstitial Lung Disease (ILD)

Fatal and nonfatal cases of interstitial lung disease (ILD) (1%) and pulmonary fibrosis have been observed in patients treated with Vectibix. Pulmonary fibrosis occurred in less than 1% (2/1467) of patients enrolled in clinical studies of Vectibix. Grade 1 ILD/pneumonitis occurred in 0.8% (1/126) of patients enrolled in clinical studies of Vectibix in combination with sotorasib.

In the event of acute onset or worsening of pulmonary symptoms, interrupt Vectibix therapy. Discontinue Vectibix therapy if ILD is confirmed.

In patients with a history of interstitial pneumonitis or pulmonary fibrosis, or evidence of interstitial pneumonitis or pulmonary fibrosis, the benefits of therapy with Vectibix versus the risk of pulmonary complications must be carefully considered.

5.7 Photosensitivity

Exposure to sunlight can exacerbate dermatologic toxicity. Advise patients to wear sunscreen and hats and limit sun exposure while receiving Vectibix.

5.8 Ocular Toxicities

Serious cases of keratitis, ulcerative keratitis, and corneal perforation have occurred with Vectibix use.

Among 585 patients who received Vectibix in combination with FOLFOX, keratitis occurred in 0.3%. In 126 patients receiving Vectibix in combination with sotorasib across clinical studies, keratitis occurred in 1.6%, ulcerative keratitis occurred in 0.8%, and vernal keratoconjunctivitis in 0.8% (all were Grade 1-2).

Monitor for evidence of keratitis, ulcerative keratitis, or corneal perforation. Interrupt or discontinue Vectibix therapy for acute or worsening keratitis, ulcerative keratitis, or corneal perforation.

5.9 Increased Mortality and Toxicity with Vectibix in Combination with Bevacizumab and Chemotherapy

In an interim analysis of an open-label, multicenter, randomized clinical trial in the first-line setting in patients with mCRC, the addition of Vectibix to the combination of bevacizumab and chemotherapy resulted in decreased OS and increased incidence of NCI-CTC Grade 3-5 (87% vs 72%) adverse reactions. NCI-CTC Grade 3-4 adverse reactions occurring at a higher rate in Vectibix-treated patients included rash/acneiform dermatitis (26% vs 1%), diarrhea (23% vs 12%), dehydration (16% vs 5%), primarily occurring in patients with diarrhea, hypokalemia (10% vs 4%), stomatitis/mucositis (4% vs < 1%), and hypomagnesemia (4% vs 0%).

NCI-CTC Grade 3-5 pulmonary embolism occurred at a higher rate in Vectibix-treated patients (7% vs 3%) and included fatal events in three (< 1%) Vectibix-treated patients.

As a result of the toxicities experienced, patients randomized to Vectibix, bevacizumab, and chemotherapy received a lower mean relative dose intensity of each chemotherapeutic agent (oxaliplatin, irinotecan, bolus 5-FU, and/or infusional 5-FU) over the first 24 weeks on study compared with those randomized to bevacizumab and chemotherapy.

5.10 Embryo-fetal Toxicity

Based on data from animal studies and its mechanism of action, Vectibix can cause fetal harm when administered to a pregnant woman. When given during organogenesis, panitumumab administration resulted in embryolethality in cynomolgus monkeys at exposures approximately 1.25 to 5 times the recommended human dose. Advise pregnant women and females of reproductive potential of the potential risk to the fetus. Advise females of reproductive potential to use effective contraception during treatment, and for at least 2 months after the last dose of Vectibix [see Use in Specific Populations (8.1, 8.3) and Clinical Pharmacology (12.1)].

6 ADVERSE REACTIONS

The following adverse reactions are discussed in greater detail in other sections of the label:

- Dermatologic and Soft Tissue Toxicity [see Boxed Warning, Dosage and Administration (2.3) and Warnings and Precautions (5.1)]
- Increased Tumor Progression, Increased Mortality, or Lack of Benefit in Patients with RAS-Mutant mCRC Receiving Vectibix Monotherapy or in Combination with Oxaliplatin-based Chemotherapy [see Indications and Usage (1) and Warnings and Precautions (5.2)]
- Electrolyte Depletion/Monitoring [see Warnings and Precautions (5.3)]
- Infusion Reactions [see Dosage and Administration (2.3) and Warnings and Precautions (5.4)]
- Acute Renal Failure [see Warnings and Precautions (5.5)]
- Pulmonary Fibrosis/Interstitial Lung Disease (ILD) [see Warnings and Precautions (5.6)]
- Photosensitivity [see Warnings and Precautions (5.7)]
- Ocular Toxicities [see Warnings and Precautions (5.8)]
- Increased Mortality and Toxicity with Vectibix in combination with Bevacizumab and Chemotherapy [see Warnings and Precautions (5.9)]

6.1 Clinical Trials Experience

Because clinical trials are conducted under widely varying conditions, adverse reaction rates in the clinical trials of a drug cannot be directly compared to rates in clinical trials of another drug and may not reflect the rates observed in practice.

The data described in WARNINGS AND PRECAUTIONS reflect exposure to Vectibix in four clinical trials in which patients received Vectibix: Study 20020408, an open-label, multinational, randomized, controlled, monotherapy clinical trial (N = 463) evaluating Vectibix with best supportive care (BSC) versus BSC alone in patients with EGFR-expressing mCRC; Study 20050203, a randomized, controlled trial (N = 1183) in patients with wild-type KRAS mCRC that evaluated Vectibix in combination with FOLFOX chemotherapy versus FOLFOX chemotherapy alone; CodeBreaK 300, a randomized controlled trial (N = 160) evaluating Vectibix in combination with sotorasib versus the investigator's choice of standard of care (trifluridine/tipiracil or regorafenib) in patients with KRAS G12C-mutated mCRC; and CodeBreak 101, an open-label, non-randomized trial evaluating sotorasib as a monotherapy and in combination with other drugs in patients with KRAS G12C-mutated advanced solid tumors, including patients with KRAS G12C-mutated mCRC who received Vectibix in combination with sotorasib (N = 79). Safety data for Study 20050203 are limited to 656 patients with wild-type KRAS mCRC. The safety profile of Vectibix in patients with wild-type RAS mCRC is similar with that seen in patients with wild-type KRAS mCRC. Safety data for CodeBreaK 300 are limited to 47 patients who received Vectibix in combination with sotorasib 960 mg.

Vectibix Monotherapy

In Study 20020408, the most common adverse reactions (≥ 20%) with Vectibix were skin rash with variable presentations, paronychia, fatigue, nausea, and diarrhea.

The most common (> 5%) serious adverse reactions in the Vectibix arm were general physical health deterioration and intestinal obstruction. The most frequently reported adverse reactions for Vectibix leading to withdrawal were general physical health deterioration (n = 2) and intestinal obstruction (n = 2).

For Study 20020408, the data described in Table 1 and in other sections below, except where noted, reflect exposure to Vectibix administered to patients with mCRC as a monotherapy at the recommended dose and schedule (6 mg/kg every 2 weeks).

Table 1. Adverse Reactions (≥ 5% Difference) Observed in Patients Treated with Vectibix Monotherapy and Best Supportive Care Compared to Best Supportive Care Alone (Study 20020408)
 | Study 20020408
System Organ Class Preferred Term | Vectibix Plus Best Supportive Care (N = 229) |  | Best Supportive Care (N = 234)
 | Any Grade n (%) | Grade 3-4 n (%) | Any Grade n (%) | Grade 3-4 n (%)
Eye Disorders
Growth of eyelashes | 13 (6)
Gastrointestinal Disorders
Nausea | 52 (23) | 2 (< 1) | 37 (16) | 1 (< 1)
Diarrhea | 49 (21) | 4 (2) | 26 (11)
Vomiting | 43 (19) | 6 (3) | 28 (12) | 2 (< 1)
Stomatitis | 15 (7) |  | 2 (< 1)
General Disorders and Administration Site Conditions
Fatigue | 60 (26) | 10 (4) | 34 (15) | 7 (3)
Mucosal inflammation | 15 (7) | 1 (< 1) | 2 (< 1)
Infections and Infestations
Paronychia | 57 (25) | 4 (2)
Respiratory, Thoracic, and Mediastinal Disorders
Dyspnea | 41 (18) | 12 (5) | 30 (13) | 8 (3)
Cough | 34 (15) | 1 (< 1) | 17 (7)
Skin and Subcutaneous Tissue Disorders
Erythema | 150 (66) | 13 (6) | 2 (< 1)
Pruritus | 132 (58) | 6 (3) | 4 (2)
Acneiform dermatitis | 131 (57) | 17 (7) | 2 (< 1)
Rash | 51 (22) | 3 (1) | 2 (< 1)
Skin fissures | 45 (20) | 3 (1) | 1 (< 1)
Exfoliative rash | 41 (18) | 4 (2)
Acne | 31 (14) | 3 (1)
Dry skin | 23 (10)
Nail disorder | 22 (10)
Skin exfoliation | 21 (9) | 2 (< 1)
Skin ulcer | 13 (6) | 1 (< 1)

Adverse reactions in Study 20020408 that did not meet the threshold criteria for inclusion in Table 1 were conjunctivitis (4.8% vs < 1%), dry mouth (4.8% vs 0%), pyrexia (16.6% vs 13.2%), chills (3.1% vs < 1%), pustular rash (4.4% vs 0%), papular rash (1.7% vs 0%), dehydration (2.6% vs 1.7%), epistaxis (3.9% vs 0%), and pulmonary embolism (1.3% vs 0%).

In Study 20020408, dermatologic toxicities occurred in 90% of patients receiving Vectibix. Skin toxicity was severe (NCI-CTC Grade 3 and higher) in 15% of patients. Ocular toxicities occurred in 16% of patients and included, but were not limited to, conjunctivitis (5%). One patient experienced an NCI-CTC Grade 3 event of mucosal inflammation. The incidence of paronychia was 25% and was severe in 2% of patients [see Warnings and Precautions (5.1)].

In Study 20020408 (N = 229), median time to the development of dermatologic, nail, or ocular toxicity was 12 days after the first dose of Vectibix; the median time to most severe skin/ocular toxicity was 15 days after the first dose of Vectibix; and the median time to resolution after the last dose of Vectibix was 98 days. Severe toxicity necessitated dose interruption in 11% of Vectibix-treated patients [see Dosage and Administration (2.3)].

Subsequent to the development of severe dermatologic toxicities, infectious complications, including sepsis, septic death, necrotizing fasciitis, and abscesses requiring incisions and drainage were reported.

Vectibix in Combination with FOLFOX Chemotherapy

The most commonly reported adverse reactions (≥ 20%) in patients with wild-type KRAS mCRC receiving Vectibix (6 mg/kg every 2 weeks) and FOLFOX therapy (N = 322) in Study 20050203 were diarrhea, stomatitis, mucosal inflammation, asthenia, paronychia, anorexia, hypomagnesemia, hypokalemia, rash, acneiform dermatitis, pruritus, and dry skin (Table 2). Serious adverse reactions (≥ 2% difference between treatment arms) in Vectibix-treated patients with wild-type KRAS mCRC were diarrhea and dehydration. The commonly reported adverse reactions (≥ 1%) leading to discontinuation in patients with wild-type KRAS mCRC receiving Vectibix were rash, paresthesia, fatigue, diarrhea, acneiform dermatitis, and hypersensitivity. One Grade 5 adverse reaction, hypokalemia, occurred in a patient who received Vectibix.

Table 2. Adverse Reactions (≥ 5% Difference) Observed in Patients with Wild-type KRAS Tumors Treated with Vectibix and FOLFOX Chemotherapy Compared to FOLFOX Chemotherapy Alone (Study 20050203)
System Organ Class Preferred Term | Vectibix Plus FOLFOX (n = 322) |  | FOLFOX Alone (n = 327)
System Organ Class Preferred Term | Any Grade n (%) | Grade 3-4 n (%) | Any Grade n (%) | Grade 3-4 n (%)
Eye Disorders
Conjunctivitis | 58 (18) | 5 (2) | 10 (3)
Gastrointestinal Disorders
Diarrhea | 201 (62) | 59 (18) | 169 (52) | 29 (9)
Stomatitis | 87 (27) | 15 (5) | 42 (13) | 1 (< 1)
General Disorders and Administration Site Conditions
Mucosal inflammation | 82 (25) | 14 (4) | 53 (16) | 1 (< 1)
Asthenia | 79 (25) | 16 (5) | 62 (19) | 11 (3)
Infections and Infestations
Paronychia | 68 (21) | 11 (3)
Investigations
Weight decreased | 58 (18) | 3 (< 1) | 22 (7)
Metabolism and Nutrition Disorders
Anorexia | 116 (36) | 14 (4) | 85 (26) | 6 (2)
Hypomagnesemia | 96 (30) | 21 (7) | 26 (8) | 1 (< 1)
Hypokalemia | 68 (21) | 32 (10) | 42 (13) | 15 (5)
Dehydration | 26 (8) | 8 (2) | 10 (3) | 5 (2)
Respiratory, Thoracic, and Mediastinal Disorders
Epistaxis | 46 (14) |  | 30 (9)
Skin and Subcutaneous Tissue Disorders
Rash | 179 (56) | 55 (17) | 24 (7) | 1 (< 1)
Acneiform dermatitis | 104 (32) | 33 (10)
Pruritus | 75 (23) | 3 (< 1) | 14 (4)
Dry skin | 68 (21) | 5 (2) | 13 (4)
Erythema | 50 (16) | 7 (2) | 14 (4)
Skin fissures | 50 (16) | 1 (< 1) | 1 (< 1)
Alopecia | 47 (15) |  | 30 (9)
Acne | 44 (14) | 10 (3) | 1 (< 1)
Nail disorder | 32 (10) | 4 (1) | 4 (1)
Palmar-plantar erythrodysesthesia syndrome | 30 (9) | 4 (1) | 9 (3) | 2 (< 1)

Adverse reactions that did not meet the threshold criteria for inclusion in Table 2 were flushing (3% vs < 1%), abdominal pain (28% vs 23%), localized infection (3.7% vs < 1%), cellulitis (2.5% vs 0%), hypocalcemia (5.6% vs 2.1%), and deep vein thrombosis (5.3% vs 3.1%).

Infusion Reactions

Infusional toxicity manifesting as fever, chills, dyspnea, bronchospasm or hypotension was assessed within 24 hours of an infusion during the clinical study. Vital signs and temperature were measured within 30 minutes prior to initiation and upon completion of the Vectibix infusion. The use of premedication was not standardized in the clinical trials. Thus, the utility of premedication in preventing the first or subsequent episodes of infusional toxicity is unknown. Across clinical trials of Vectibix monotherapy, 3% (24/725) experienced infusion reactions of which < 1% (3/725) were severe (NCI-CTC Grade 3-4). In one patient, Vectibix was permanently discontinued for a serious infusion reaction [see Dosage and Administration (2.2, 2.3)].

Vectibix in Combination with Sotorasib

The safety of Vectibix in combination with sotorasib was evaluated in the CodeBreaK 300 study [see Clinical Studies (14.4)]. Patients with KRAS G12C-mutated mCRC received Vectibix 6 mg/kg intravenous every 2 weeks in combination with sotorasib 960 mg orally once daily (N = 47), Vectibix 6 mg/kg intravenous every 2 weeks in combination with sotorasib 240 mg orally once daily (N = 50), or the investigator's choice of standard of care (SOC) consisting of trifluridine/tipiracil or regorafenib (N = 50). Among the 47 patients who received Vectibix in combination with sotorasib 960 mg, 36% were exposed to Vectibix for 6 months or longer and 4.3% were exposed for greater than 12 months.

The median age of patients who received Vectibix in combination with sotorasib 960 mg was 63 years (range: 37-79 years); 38% were age 65 years or older; 49% were female; 79% were White, and 13% were Asian.

Serious adverse reactions occurred in 26% of patients receiving Vectibix in combination with sotorasib 960 mg. Serious adverse reactions in ≥ 2 patients receiving Vectibix in combination with sotorasib 960 mg were sepsis (6%) and intestinal obstruction (4.3%). Fatal adverse reactions occurred in 2 patients (4.3%) receiving Vectibix in combination with sotorasib 960 mg, consisting of cardiac arrest and sepsis (1 patient each).

Permanent discontinuation of Vectibix due to an adverse reaction occurred in 1 patient for decreased corrected calcium.

Dosage interruptions of Vectibix due to an adverse reaction occurred in 38% of patients. Adverse reactions which required dosage interruption in ≥ 2 patients were rash, hypomagnesemia, and keratitis.

Dosage reductions of Vectibix due to an adverse reaction occurred in 17% of patients. The adverse reaction which required dose reduction in ≥ 2 patients was rash.

The most common adverse reactions (≥ 20%) in patients receiving Vectibix in combination with sotorasib 960 mg were rash, dry skin, diarrhea, stomatitis, fatigue and musculoskeletal pain.

The most common Grade 3 or 4 laboratory abnormalities in ≥ 2 patients (4.3%) were decreased magnesium, decreased potassium, decreased corrected calcium, and increased potassium.

Table 3 and Table 4 summarize the adverse reactions and laboratory abnormalities, respectively, identified in CodeBreaK 300.

Table 3. Adverse Reactions (≥ 10%) in Patients with KRAS G12C-Mutated CRC who Received Vectibix in Combination with Sotorasib in CodeBreaK 300
Adverse Reaction | Vectibix 6 mg/kg in combination with sotorasib 960 mg N = 47 |  | Trifluridine/tipiracil or regorafenib N = 50
Adverse Reaction | All Grades (%) | Grade 3 or 4 (%) | All Grades (%) | Grade 3 or 4 (%)
Skin and Subcutaneous Tissue Disorders
Rash [Rash includes dermatitis acneiform, dermatosis, drug eruption, eczema, erythema, hand dermatitis, rash, rash erythematous, rash maculo-papular, rash papular, rash pruritic, rash pustular, and skin toxicity.] | 87 | 26 | 8 | 2
Dry skin [Dry skin includes dry skin, xerosis, and xeroderma.] | 28 | 0 | 2 | 0
Pruritis | 17 | 0 | 4 | 0
Nail Disorder [Nail disorders include nail avulsion, nail cuticle fissure, nail disorder, nail toxicity, and paronychia.] | 17 | 0 | 0 | 0
Skin fissure | 13 | 0 | 0 | 0
Palmar-plantar erythrodysesthesia syndrome | 13 | 0 | 10 | 4
Gastrointestinal Disorders
Diarrhea [Diarrhea includes diarrhea, gastroenteritis, and diarrhea hemorrhagic.] | 28 | 6 | 26 | 0
Stomatitis [Stomatitis includes mucosal inflammation, stomatitis, mouth ulceration, angular cheilitis, and cheilitis.] | 26 | 0 | 14 | 0
Nausea | 17 | 2.1 | 36 | 4
Constipation | 15 | 2.1 | 10 | 0
Abdominal pain [Abdominal pain includes abdominal pain, abdominal pain upper, abdominal pain lower, abdominal discomfort, and hepatic pain.] | 15 | 0 | 18 | 2
Vomiting | 13 | 2.1 | 10 | 2
General disorders
Fatigue [Fatigue includes asthenia and fatigue.] | 21 | 0 | 34 | 2
Musculoskeletal and Connective Tissue Disorders
Musculoskeletal pain [Musculoskeletal pain includes arthralgia, back pain, myalgia, musculoskeletal chest pain, bone pain, and pain in extremity.] | 21 | 2.1 | 14 | 2
Hematological Disorders
Hemorrhage [Hemorrhage includes epistaxis, gastrointestinal hemorrhage, vaginal hemorrhage, rectal hemorrhage, hematochezia, hemorrhage, hemorrhage urinary tract, hematospermia, and hematuria.] | 13 | 2.1 | 2 | 0
Eye Disorders
Conjunctivitis [Conjunctivitis includes conjunctival hyperemia, conjunctivitis, and conjunctivitis allergic.] | 11 | 0 | 2 | 0

Table 4. Select Laboratory Abnormalities (≥ 20%) that Worsened from Baseline in Patients with KRAS G12C-Mutated CRC who Received Vectibix in Combination with Sotorasib in CodeBreaK 300 [The denominator used to calculate the rate varied from 44 to 46 in the Vectibix + sotorasib arm and 18 to 50 in the trifluridine/tipiracil or regorafenib arm based on the number of patients with a baseline value and at least one post-treatment value.]
Laboratory Abnormalities | Vectibix 6 mg/kg + Sotorasib |  | Trifluridine/tipiracil or Regorafenib
Laboratory Abnormalities | All Grades (%) | Grade 3 or 4 (%) | All Grades (%) | Grade 3 or 4 (%)
Chemistry
Magnesium decreased | 76 | 24 | 8 | 0
Calcium (corrected) decreased | 74 | 4.3 | 46 | 0
Aspartate aminotransferase increased | 39 | 0 | 22 | 2
Alkaline phosphatase increased | 33 | 2.2 | 33 | 0
Creatinine kinase increased | 30 | 2.3 | 7 | 0
Alanine aminotransferase increased | 28 | 0 | 16 | 2
Potassium decreased | 26 | 7 | 12 | 0
Albumin decreased | 26 | 2.2 | 22 | 0
Urine protein increased | 23 | 0 | 22 | 6
Potassium increased | 22 | 4.3 | 6 | 0
Glucose decreased | 22 | 0 | 2 | 0
Hematology
Hemoglobin decreased | 30 | 0 | 58 | 6
Lymphocytes decreased | 26 | 2.2 | 56 | 8
White blood cells decreased | 24 | 0 | 48 | 14

6.2 Postmarketing Experience

The following adverse reactions have been identified during post-approval use of Vectibix. Because these reactions are reported in a population of uncertain size, it is not always possible to reliably estimate their frequency or establish a causal relationship to drug exposure.

- Skin and subcutaneous tissue disorders: Skin necrosis, angioedema, life-threatening and fatal bullous mucocutaneous disease [see Boxed Warning, Dosage and Administration (2.3) and Warnings and Precautions (5.1)]
- Immune system disorders: Infusion reaction [see Dosage and Administration (2.3) and Warnings and Precautions (5.4)]
- Eye disorders: Keratitis/ulcerative keratitis, corneal perforation [see Warnings and Precautions (5.8)]

8 USE IN SPECIFIC POPULATIONS

8.1 Pregnancy

Risk Summary

Based on data from animal studies and its mechanism of action, Vectibix can cause fetal harm when administered to pregnant women [see Clinical Pharmacology (12.1)]. Limited available data on the use of Vectibix in pregnant women are not sufficient to inform a risk of adverse pregnancy-related outcomes. Vectibix is a human IgG monoclonal antibody and may be transferred across the placenta during pregnancy. Reproduction studies in cynomolgus monkeys treated with 1.25 to 5 times the recommended human dose of panitumumab resulted in significant embryolethality and abortions; however, no other evidence of teratogenesis was noted in offspring [see Data]. Advise pregnant women of the potential risk to the fetus.

In the U.S. general population, the estimated background risk of major birth defects and miscarriage in clinically recognized pregnancies is 2-4% and 15-20%, respectively.

Data

Animal Data

Based on animal models, EGFR is involved in prenatal development and may be essential for normal organogenesis, proliferation, and differentiation in the developing embryo. Pregnant cynomolgus monkeys were treated weekly with panitumumab during the period of organogenesis (gestation day [GD] 20-50). While no panitumumab was detected in serum of neonates from panitumumab-treated dams, anti-panitumumab antibody titers were present in 14 of 27 offspring delivered at GD 100. There were no fetal malformations or other evidence of teratogenesis noted in the offspring; however, significant increases in embryolethality and abortions occurred at doses of approximately 1.25 to 5 times the recommended human dose (based on body weight).

8.2 Lactation

Risk Summary

There are no data on the presence of panitumumab in human milk or the effects of panitumumab on the breastfed infant or on milk production. Human IgG is present in human milk, but published data suggest that breast milk antibodies do not enter the neonatal and infant circulation in substantial amounts. Because of the potential for serious adverse reactions in breastfed infants from Vectibix, advise women not to breastfeed during treatment with Vectibix and for 2 months after the last dose.

8.3 Females and Males of Reproductive Potential

Contraception

Females

Vectibix can cause fetal harm when administered to a pregnant woman [see Use in Specific Populations (8.1)]. Advise females of reproductive potential to use effective contraception during treatment with Vectibix and for 2 months after the last dose of Vectibix.

Infertility

Females

Based on results from animal fertility studies conducted in female cynomolgus monkeys, Vectibix may reduce fertility in females of reproductive potential. The effects in animal studies were reversible [see Nonclinical Toxicology (13.1)].

8.4 Pediatric Use

The safety and effectiveness of Vectibix have not been established in pediatric patients.

The pharmacokinetics of panitumumab at doses ranging from 2.5 mg/kg intravenous weekly, 6 mg/kg intravenous every 2 weeks, or 9 mg/kg intravenous every 3 weeks were evaluated in 28 pediatric patients. Panitumumab exposures were comparable in adult and adolescent patients of 12 to 17 years of age. Limited data suggested that pediatric patients of 2 to < 12 years of age had lower panitumumab exposure and higher clearance than that in adolescent patients following 6 mg/kg intravenous administration of Vectibix. There was no evidence of an anti-tumor treatment effect in these patients.

8.5 Geriatric Use

Of the 737 patients who received Vectibix monotherapy for recurrent or refractory mCRC [see Clinical Studies (14.1)], 36% were 65 and over while 8% were 75 and over. No overall differences in safety or efficacy were observed in elderly patients (≥ 65 years of age) treated with Vectibix monotherapy.

Of the 322 patients who received Vectibix plus FOLFOX, for wild-type KRAS-mutated mCRC [see Clinical Studies (14.2)], 128 (40%) were 65 and over while 8% were 75 and over. Patients older than 65 years of age experienced an increased incidence of serious adverse events (52% vs 36%) and an increased incidence of serious diarrhea (15% vs 5%) as compared to younger patients.

In a pooled analysis of 132 patients who received Vectibix in combination with sotorasib 960 mg for KRAS G12C-mutated mCRC, 30% were 65 and over while 9% were 75 and over. No overall differences in safety or efficacy were observed in elderly patients (≥ 65 years of age) compared to younger patients treated with Vectibix in combination with sotorasib.

10 OVERDOSAGE

Doses up to approximately twice the recommended therapeutic dose (12 mg/kg) resulted in adverse reactions of skin toxicity, diarrhea, dehydration, and fatigue.

11 DESCRIPTION

Panitumumab is an epidermal growth factor receptor (EGFR) antagonist for intravenous use. Panitumumab is a human IgG2 kappa monoclonal antibody with an approximate molecular weight of 147 kDa that is produced in genetically engineered mammalian (Chinese hamster ovary) cells.

Vectibix (panitumumab) Injection for intravenous use is a sterile, colorless solution with a pH range of 5.6 to 6.0, which may contain a small amount of visible translucent-to-white, amorphous, proteinaceous particles. Each single-dose 5 mL vial contains 100 mg of panitumumab, 34 mg sodium acetate, 29 mg sodium chloride, and Water for Injection, USP. Each single-dose 20 mL vial contains 400 mg of panitumumab, 136 mg sodium acetate, 117 mg sodium chloride, and Water for Injection, USP.

12 CLINICAL PHARMACOLOGY

12.1 Mechanism of Action

The EGFR is a transmembrane glycoprotein that is a member of a subfamily of type I receptor tyrosine kinases, including EGFR, HER2, HER3, and HER4. EGFR is constitutively expressed in normal epithelial tissues, including the skin and hair follicle. EGFR is overexpressed in certain human cancers, including colon and rectum cancers. Interaction of EGFR with its normal ligands (e.g., EGF, transforming growth factor-alpha) leads to phosphorylation and activation of a series of intracellular proteins, which in turn regulate transcription of genes involved with cellular growth and survival, motility, and proliferation. KRAS (Kirsten rat sarcoma 2 viral oncogene homologue) and NRAS (Neuroblastoma RAS viral oncogene homologue) are highly related members of the RAS oncogene family. Signal transduction through the EGFR can result in activation of the wild-type KRAS and NRAS proteins; however, in cells with activating RAS somatic mutations, the RAS-mutant proteins are continuously active and appear independent of EGFR regulation.

Panitumumab binds specifically to EGFR on both normal and tumor cells, and competitively inhibits the binding of ligands for EGFR. Nonclinical studies show that binding of panitumumab to the EGFR prevents ligand-induced receptor autophosphorylation and activation of receptor-associated kinases, resulting in inhibition of cell growth, induction of apoptosis, decreased proinflammatory cytokine and vascular growth factor production, and internalization of the EGFR. In vitro assays and in vivo animal studies demonstrate that panitumumab inhibits the growth and survival of selected human tumor cell lines expressing EGFR.

In the setting of KRAS G12C-mutant CRC, EGFR activation has been identified as a mechanism of resistance to KRAS G12C inhibition. In a murine patient-derived colorectal tumor xenograft model, the combination of panitumumab and sotorasib, a KRAS G12C inhibitor, had increased antitumor activity compared to either panitumumab or sotorasib alone.

12.3 Pharmacokinetics

Panitumumab administered as a monotherapy exhibits nonlinear pharmacokinetics.

Following single-dose administrations of panitumumab as 1-hour infusions, the area under the concentration-time curve (AUC) increased in a greater than dose-proportional manner, and clearance (CL) of panitumumab decreased from 30.6 to 4.6 mL/day/kg as the dose increased from 0.75 to 9 mg/kg. However, at doses above 2 mg/kg, the AUC of panitumumab increased in an approximately dose-proportional manner.

Following the recommended dose regimen (6 mg/kg given once every 2 weeks as a 1-hour infusion), panitumumab concentrations reached steady-state levels by the third infusion with mean (± SD) peak and trough concentrations of 213 ± 59 and 39 ± 14 mcg/mL, respectively. The mean (± SD) AUC0-tau and CL were 1306 ± 374 mcg•day/mL and 4.9 ± 1.4 mL/kg/day, respectively. The elimination half-life was approximately 7.5 days (range: 3.6 to 10.9 days).

No clinically significant differences in the pharmacokinetics of panitumumab were observed based on age (21 to 88 years), sex, race (White, Black, and Asian), mild or moderate renal impairment (CrCL 30 to 89 mL/min), mild or moderate hepatic impairment (total bilirubin ≤ 3 × ULN and any AST), and EGFR membrane-staining intensity (1+, 2+, and 3+) in tumor cells.

12.6 Immunogenicity

The observed incidence of anti-drug antibodies is highly dependent on the sensitivity and specificity of the assay. Differences in assay methods preclude meaningful comparisons of the incidence of anti-drug antibodies in the studies described below with the incidence of anti-drug antibodies in other studies, including those of Vectibix or of other panitumumab products.

During the 23-week treatment period of Vectibix as a monotherapy in Studies 20080763, 20020408, 20030194 and other clinical trials, the incidence of anti-panitumumab antibodies was 5.2% (74/1417). Of the 74 patients who tested positive for anti-panitumumab antibodies, 18.9% (14/74) had neutralizing antibodies against panitumumab.

During the 23-week treatment period of Vectibix in combination with chemotherapy in Studies 20050203, 20070509, 20050181 and other clinical trials, the incidence of anti-panitumumab antibodies was 3.2% (47/1470). Of the 47 patients who tested positive for anti-panitumumab antibodies, 14.9% (7/47) had neutralizing antibodies against panitumumab.

There was no identified clinically significant effect of anti-panitumumab-antibodies on panitumumab pharmacokinetics following monotherapy. The effect of anti-panitumumab antibodies on the pharmacokinetics, following combination therapy, and on the safety and effectiveness of panitumumab has not been fully characterized.

13 NONCLINICAL TOXICOLOGY

13.1 Carcinogenesis, Mutagenesis, Impairment of Fertility

No carcinogenicity or mutagenicity studies of panitumumab have been conducted. It is not known if panitumumab can impair fertility in humans. Prolonged menstrual cycles and/or amenorrhea occurred in normally cycling, female cynomolgus monkeys treated weekly with 1.25 to 5 times the recommended human dose of panitumumab (based on body weight). Menstrual cycle irregularities in panitumumab-treated female monkeys were accompanied by both a decrease and delay in peak progesterone and 17β-estradiol levels. Normal menstrual cycling resumed in most animals after discontinuation of panitumumab treatment. A no-effect level for menstrual cycle irregularities and serum hormone levels was not identified. The effects of panitumumab on male fertility have not been studied; however, no adverse effects were observed microscopically in reproductive organs from male cynomolgus monkeys treated for 26 weeks with panitumumab at doses of up to approximately 5-fold the recommended human dose (based on body weight).

14 CLINICAL STUDIES

14.1 Recurrent or Refractory mCRC

The safety and efficacy of Vectibix was demonstrated in Study 20020408, an open-label, multinational, randomized, controlled trial of 463 patients with EGFR-expressing, metastatic carcinoma of the colon or rectum, in Study 20080763, an open-label, multicenter, multinational, randomized trial of 1010 patients with wild-type KRAS mCRC, and in Study 20100007, an open-label, multicenter, multinational, randomized trial of 377 patients with wild-type KRAS mCRC.

Study 20020408 (NCT00113763)

Patients in Study 20020408 were required to have progressed on or following treatment with a regimen(s) containing a fluoropyrimidine, oxaliplatin, and irinotecan; progression was confirmed by an independent review committee (IRC) masked to treatment assignment for 76% of the patients. Patients were randomized (1:1) to receive panitumumab at a dose of 6 mg/kg given once every 2 weeks plus BSC (N = 231) or BSC alone (N = 232) until investigator-determined disease progression. Randomization was stratified based on Eastern Cooperative Oncology Group (ECOG) performance status (PS) (0 and 1 vs 2) and geographic region (Western Europe, Eastern/Central Europe, or other). Upon investigator-determined disease progression, patients in the BSC-alone arm were eligible to receive panitumumab and were followed until disease progression was confirmed by the IRC.

Based upon IRC determination of disease progression, a statistically significant prolongation in progression free survival (PFS) was observed in patients receiving panitumumab compared to those receiving BSC alone. The mean PFS was 96 days in the panitumumab arm and 60 days in the BSC-alone arm.

The study results were analyzed in the wild-type KRAS subgroup where KRAS status was retrospectively determined using archived paraffin-embedded tumor tissue. KRAS mutation status was determined in 427 patients (92%); of these, 243 (57%) had no detectable KRAS mutations in either codons 12 or 13. The hazard ratio for PFS in patients with wild-type KRAS mCRC was 0.45 (95% CI: 0.34-0.59) favoring the panitumumab arm. The response rate was 17% for the panitumumab arm and 0% for BSC. There were no differences in OS; 77% of patients in the BSC arm received panitumumab at the time of disease progression.

Study 20080763 (NCT01001377)

Study 20080763 was an open-label, multicenter, multinational, randomized (1:1) clinical trial, stratified by region (North America, Western Europe, and Australia versus rest of the world) and ECOG PS (0 and 1 vs 2) in patients with wild-type KRAS mCRC. A total of 1010 patients who received prior treatment with irinotecan, oxaliplatin, and a thymidylate synthase inhibitor were randomized to receive Vectibix 6 mg/kg intravenously over 60 minutes every 14 days or cetuximab 400 mg/m^2 intravenously over 120 minutes on day 1 followed by 250 mg/m^2 intravenously over 60 minutes every 7 days. The trial excluded patients with clinically significant cardiac disease and interstitial lung disease. The major efficacy analysis tested whether the OS of Vectibix was noninferior to cetuximab. Data for investigator-assessed PFS and objective response rate (ORR) were also collected. The criteria for noninferiority was for Vectibix to retain at least 50% of the OS benefit of cetuximab based on an OS hazard ratio of 0.55 from the NCIC CTG CO.17 study relative to BSC.

In Study 20080763, 37% of patients were women, 52% were white, 45% were Asian, and 1.3% were Hispanic or Latino. Thirty-one percent of patients were enrolled at sites in North America, Western Europe, or Australia. ECOG performance was 0 in 32% of patients, 1 in 60% of patients, and 2 in 8% of patients. Median age was 61 years. More patients (62%) had colon cancer than rectal cancer (38%). Most patients (74%) had not received prior bevacizumab.

The key efficacy analysis for Study 20080763 demonstrated that Vectibix was statistically significantly noninferior to cetuximab for OS.

The efficacy results for Study 20080763 are presented in Table 5 and Figure 1.

Table 5. Results in Previously Treated Wild-type KRAS mCRC (Study 20080763)
Wild-type KRAS Population | Vectibix (n = 499) [Modified intent-to-treat population that included all patients who received at least one dose of therapy] | Cetuximab (n = 500)
Overall Survival (OS)
Number of OS events (%) | 383 (76.8) | 392 (78.4)
Median (months) (95% CI) | 10.4 (9.4, 11.6) | 10.0 (9.3, 11.0)
Hazard ratio (95% CI) | 0.97 (0.84, 1.11)
Progression-Free Survival (PFS)
Median (months) (95% CI) | 4.1 (3.2, 4.8) | 4.4 (3.2, 4.8)
Hazard ratio (95% CI) | 1.00 (0.88, 1.14)
Objective Response Rate (ORR)
% (95% CI) | 22% (18%, 26%) | 19% (16%, 23%)

Figure 1. Kaplan-Meier Plot of Overall Survival in Patients with Wild-type KRAS mCRC (Study 20080763)

Study 20100007 (NCT01412957)

Study 20100007 was an open-label, multicenter, randomized (1:1) clinical study stratified by ECOG performance status (0 or 1 vs 2) and region (sites in Europe versus Asia versus rest of world) in patients with wild-type KRAS mCRC. Eligible patients were required to have received prior therapy with irinotecan, oxaliplatin, and a thymidylate synthase inhibitor, and have wild-type KRAS exon 2 mCRC as determined by a clinical trial assay. An assessment for RAS status (defined as KRAS exons 2, 3, and 4 and NRAS exons 2, 3, and 4) using Sanger sequencing was conducted in patients for whom tumor tissue was available.

Patients were randomized to receive Vectibix (6 mg/kg intravenously every 14 days) plus BSC or BSC alone. Patients received Vectibix and BSC or BSC until disease progression, withdrawal of consent, unacceptable toxicity, or death. Patients randomized to BSC were not offered Vectibix at the time of disease progression. The major efficacy outcome measure was OS in patients with wild-type KRAS mCRC. Secondary efficacy outcome measures included OS in the subgroup of patients with wild-type RAS mCRC; PFS and ORR in patients with wild-type KRAS; and PFS and ORR in the subgroup of patients with wild-type RAS mCRC.

A total of 377 patients were randomized, 189 to the Vectibix plus BSC arm and 188 to the BSC alone arm. Baseline demographics and disease characteristics were: median age of 61 years (range: 19-82); 57% male; 55% White, 43% Asian; 36% ECOG PS-0, 55% ECOG PS-1; 57% had a primary colon tumor and 43% had a primary rectal tumor; and 32% had prior bevacizumab exposure.

KRAS tumor mutation status was available for all patients and RAS tumor mutation status was available for 86% of the 377 patients. Among the 377 patients, 270 (72%) patients had wild-type RAS tumors, 54 (14%) had mutant RAS tumors, and 54 (14%) had unknown RAS tumor status.

The results of the study demonstrated a statistically significant improvement in OS. The efficacy results for Study 20100007 are presented in Table 6 and Figure 2.

Table 6. Results in Previously Treated Wild-type KRAS and Wild-type RAS mCRC (Study 20100007)
 | Wild-type KRAS Population (n = 377) |  | Wild-type RAS Population (n = 270)
 | Vectibix Plus BSC (n = 189) | BSC (n = 188) | Vectibix Plus BSC (n = 142) | BSC (n = 128)
OS
Number of deaths (%) | 136 (72) | 135 (72) | 104 (73) | 95 (74)
Median (months) (95% CI) | 10 (8.7, 11.4) | 7.4 (5.8, 9.3) | 10 (8.7, 11.6) | 6.9 (5.2, 7.9)
HR (95% CI) | 0.73 (0.57, 0.93) |  | 0.7 (0.53, 0.93)
p-value | 0.0096 |  | 0.0135
PFS
Number of events (%) | 182 (96) | 162 (86) | 137 (97) | 113 (88)
Median (months) (95% CI) | 3.6 (3.4, 5.3) | 1.7 (1.6, 1.9) | 5.2 (3.5, 5.3) | 1.7 (1.6, 2.2)
HR (95% CI) | 0.51 (0.41, 0.64) |  | 0.46 (0.35. 0.59)
p-value | < 0.0001 |  | < 0.0001
ORR % (95% CI) | 27 (20.8, 33.9) | 1.6 (0.3, 4.6) | 31 (23.5, 39.3) | 2.3 (0.5, 6.7)

Figure 2. Kaplan-Meier Plot of Overall Survival in Patients with Wild-type RAS mCRC (Study 20100007)

14.2 First-line mCRC in Combination with FOLFOX Chemotherapy

Study 20050203 (NCT00364013)

Study 20050203 was a multicenter, open-label trial that randomized (1:1) patients with mCRC who were previously untreated in the metastatic setting and who had received no prior oxaliplatin to receive Vectibix every 14 days in combination with FOLFOX or to FOLFOX alone every 14 days. Vectibix was administered at 6 mg/kg over 60 minutes prior to administration of chemotherapy. The FOLFOX regimen consisted of oxaliplatin 85 mg per m^2 IV infusion over 120 minutes and leucovorin (dl-racemic) 200 mg per m^2 intravenous infusion over 120 minutes at the same time on day 1 using a Y-line, followed on day 1 by 5-FU 400 mg per m^2 intravenous bolus. The 5-FU bolus was followed by a continuous infusion of 5-FU 600 mg per m^2 over 22 hours. On day 2, patients received leucovorin 200 mg per m^2 followed by the bolus dose (400 mg per m^2) and continuous infusion of 5-FU (600 mg per m^2) over 22 hours. Study 20050203 excluded patients with known central nervous system metastases, clinically significant cardiac disease, interstitial lung disease, or active inflammatory bowel disease. The prespecified major efficacy measure was PFS in the subgroup of patients with wild-type KRAS mCRC as assessed by a blinded independent central review of imaging. Other key efficacy measures included OS and ORR.

In Study 20050203, in the wild-type KRAS subgroup (n = 656), 64% of patients were men, 92% White, 2% Black, and 4% Hispanic or Latino. Sixty-six percent of patients had colon cancer and 34% had rectal cancer. ECOG performance was 0 in 56% of patients, 1 in 38% of patients, and 2 in 6% of patients. Median age was 61.5 years.

The efficacy results in Study 20050203 in patients with wild-type KRAS mCRC are presented in Table 7 below.

Table 7. Results in Patients with Wild-type KRAS mCRC (Study 20050203)
Wild-type KRAS population | Primary Analysis
Wild-type KRAS population | Vectibix plus FOLFOX (n = 325) | FOLFOX Alone (n = 331)
PFS
Median (months) (95% CI) | 9.6 (9.2, 11.1) | 8 (7.5, 9.3)
Hazard ratio (95% CI) p-value | 0.8 (0.66, 0.97) p = 0.02
ORR
% (95% CI) | 54% (48%, 59%) | 47% (41%, 52%)

Exploratory Analysis of OS

An exploratory analysis of OS with updated information based on events in 82% of patients with wild-type KRAS mCRC estimated the treatment effect of Vectibix plus FOLFOX compared with FOLFOX alone on OS (Figure 3). Median OS among 325 patients with wild-type KRAS mCRC who received Vectibix plus FOLFOX was 23.8 months (95% CI: 20.0, 27.7) vs 19.4 months (95% CI: 17.4, 22.6) among 331 patients who received FOLFOX alone (HR = 0.83, 95% CI: 0.70, 0.98).

Figure 3. Kaplan-Meier Plot of Overall Survival in Patients with Wild-type KRAS mCRC (Study 20050203)

Retrospective exploratory analyses in the RAS wild-type subgroup

Among the 656 patients with wild-type KRAS exon 2 mCRC, RAS mutation status was assessed for 620 patients using Sanger bidirectional sequencing and Surveyor®/WAVE® analysis. Of these 620 patients, approximately 17% of patients (n = 104) tumors harbored mutations in KRAS exons 3 or 4 or in NRAS exons 2, 3, and 4.

Retrospective subset analyses were then conducted among the subset of patients without RAS mutations (n = 512) as described above.

In the wild-type RAS subgroup, 65% of patients were men and 91% were White, 2% Black, and 5% Hispanic or Latino. Sixty-five percent of patients had colon cancer and 35% had rectal cancer. ECOG performance was 0 in 57% of patients, 1 in 37% of patients, and 2 in 6% of patients. Median age was 61 years.

Table 8. Results in Patients with Wild-Type RAS mCRC (Study 20050203)
Wild-type RAS population | Primary Analysis
Wild-type RAS population | Vectibix plus FOLFOX (n = 259) | FOLFOX Alone (n = 253)
PFS
Median (months) (95% CI) | 10.1 (9.3, 12.0) | 7.9 (7.2, 9.3)
Hazard ratio (95% CI) | 0.72 (0.58, 0.90)
OS [OS with updated information based on events in 82% of patients]
Median (months) (95% CI) | 25.8 (21.7; 29.7) | 20.2 (17.5; 23.6)
Hazard ratio (95% CI) | 0.77 (0.64; 0.94)
ORR
% (95% CI) | 58% (51%, 64%) | 45% (39%, 51%)

Figure 4. Kaplan-Meier Plot of Overall Survival in Patients with Wild-Type RAS-mCRC (Study 20050203)

14.3 RAS-Mutant mCRC

Vectibix is not effective for the treatment of patients with RAS-mutant mCRC, defined as a RAS mutation in exon 2 (codons 12 and 13), exon 3 (codons 59 and 61), or exon 4 (codons 117 and 146) of KRAS and NRAS, except for when Vectibix is used in combination with sotorasib in KRAS G12C-mutated mCRC.

In Study 20050203, among patients with RAS-mutant tumors, the median PFS was 7.3 months (95% CI: 6.3, 7.9) among 272 patients receiving Vectibix plus FOLFOX and 8.7 months (95% CI: 7.6, 9.4) among patients who received FOLFOX alone (HR = 1.31, 95% CI: 1.07, 1.60). The median OS was 15.6 months (95% CI: 13.4, 17.9) among patients receiving Vectibix plus FOLFOX and 19.2 months (95% CI: 16.7, 21.8) among patients who received FOLFOX alone (HR = 1.25, 95% CI: 1.02, 1.55).

In Study 20100007, among patients with RAS-mutant tumors, no differences in OS or PFS were observed between the treatment arms [n = 54; OS HR = 0.99 (95% CI: 0.49, 2.00); PFS HR = 1.03 (95% CI: 0.56, 1.90)].

14.4 KRAS G12C-mutated mCRC

The efficacy of Vectibix in combination with sotorasib was evaluated in CodeBreaK 300 [NCT 05198934], a multicenter, randomized, open-label, active-controlled study conducted in previously treated patients with KRAS G12C-mutated mCRC. Key eligibility criteria included patients 18 years of age or older, who had received at least one prior line of therapy for mCRC, and who had received prior fluoropyrimidine, oxaliplatin, and irinotecan for metastatic disease unless there was a medical contraindication.

All patients were also required to have KRAS G12C-mutated mCRC prospectively identified in tumor tissue samples using the QIAGEN therascreen® KRAS RGQ PCR performed in a central laboratory. Other eligibility criteria included an ECOG PS of ≤ 2, and at least one measurable lesion as defined by Response Evaluation Criteria in Solid Tumors (RECIST v1.1).

A total of 160 patients with previously treated mCRC with the KRAS G12C mutation were randomized 1:1:1 to receive Vectibix 6 mg/kg intravenously every 2 weeks and sotorasib 960 mg orally daily (N = 53), or Vectibix 6 mg/kg intravenously every 2 weeks and sotorasib 240 mg orally daily (N = 53), or investigator's choice of SOC consisting of trifluridine/tipiracil, or regorafenib (N = 54). Randomization was stratified by prior anti-angiogenic therapy (yes or no), time from initial diagnosis of metastatic disease to randomization (≥ 18 months; < 18 months), and ECOG status (0 or 1 versus 2). Patients received treatment until disease progression, lack of clinical benefit or intolerance to treatment. Sotorasib discontinuation required Vectibix discontinuation [see Dosage and Administration (2.3)].

The major efficacy outcome measure was PFS as evaluated by Blinded Independent Central Review (BICR) according to RECIST 1.1. Additional efficacy outcome measures included OS, Overall Response Rate (ORR), and duration of response (DOR). The efficacy results presented below are limited to Vectibix in combination with the recommended sotorasib dosage of 960 mg daily.

Of the 107 patients randomized to either Vectibix in combination with sotorasib 960 mg once daily or the control arm, the median age was 64 years (range: 34-81 years); 46% were age 65 years or older; 50% were female; 74% were White; 17% were Asia; and 97% of the patients had ECOG PS 0 or 1. The primary site of disease was colon (69%) or rectum (31%). The median number of prior lines of therapy for metastatic disease was 2. Of these patients, 100% received prior fluoropyrimidine, 99% received prior oxaliplatin, 93% received prior irinotecan and 18% of patients had received prior trifluridine/tipiracil, or regorafenib.

The trial demonstrated a statistically significant improvement in PFS for patients randomized to Vectibix in combination with sotorasib 960 mg compared to the investigator's choice SOC. The final analysis of OS was not statistically significant.

The final analysis of PFS for patients randomized to Vectibix in combination with sotorasib 240 mg compared to investigator's choice of SOC was not statistically significant.

The efficacy results from CodeBreaK 300 are summarized in Table 9 and Figure 5.

Table 9. Efficacy Results for Patients with KRAS G12C-mutated CRC in CodeBreaK 300
Efficacy Parameters | Vectibix 6 mg/kg + Sotorasib 960 mg QD (N = 53) | SOC (trifluridine and tipiracil, or regorafenib) (N = 54)
Progression-Free Survival (PFS) per BICR
Number of events (%) | 32 (60) | 35 (65)
Median in months (95% CI) | 5.6 (4.2, 6.3) | 2 (1.9, 3.9)
Hazard ratio (95% CI) [Hazard ratios and 95% CIs were estimated using a stratified Cox proportional hazards model.] | 0.48 (0.3, 0.78)
p-value (2-sided) [p-value was calculated using a stratified log-rank test.] | 0.005
Overall Survival (OS) [OS analysis was based on 6 months additional follow-up data from the time of PFS primary analysis.]
Deaths (%) | 24 (45) | 30 (56)
Median in months (95% CI) | NR (8.6, NR) | 10.3 (7, NR)
Hazard ratio (95% CI) | 0.7 (0.41, 1.18)
Overall Response Rate (ORR) per BICR
ORR (%) (95% CI) [95% CIs were estimated using the Clopper-Pearson method.] | 26 (15, 40) | 0 (0, 7)
CR, n (%) | 1 (1.9) | 0
PR, n (%) | 13 (25) | 0
Duration of Response (DOR)
Median in months (range) [For DOR + indicates censored subjects.] | 4.4 (1.9+, 6+) | -
N = number of randomized subjects, NR = not reached, QD = once daily, SOC = standard of care, CR = complete response, PR = partial response, BICR = Blinded Independent Central Review Committee, CI = confidence interval.

Figure 5. Kaplan-Meier Curve for Progression-Free Survival in CodeBreaK 300

16 HOW SUPPLIED/STORAGE AND HANDLING

Vectibix is supplied as a sterile, colorless, preservative-free solution containing 20 mg/mL panitumumab in a single-dose vial. Vectibix is provided as one vial per carton.

- Each 5 mL single-dose vial contains 100 mg of panitumumab in 5 mL (20 mg/mL) (NDC 55513-954-01, NDC 55513-954-21).
- Each 20 mL single-dose vial contains 400 mg of panitumumab in 20 mL (20 mg/mL) (NDC 55513-956-01, NDC 55513-956-21).

STORAGE AND HANDLING

Store vials in the original carton under refrigeration at 2° to 8°C (36° to 46°F) until time of use. Protect from direct sunlight. Do not freeze or shake. Discard any unused portion remaining in the vial.

17 PATIENT COUNSELING INFORMATION

Discuss the following with patients prior to treatment with Vectibix:

Skin and eye disorders:

Advise patients to contact a healthcare professional if they experience skin or ocular/visual changes [see Boxed Warning, Dosage and Administration (2.3), Warnings and Precautions (5.1, 5.8) and Adverse Reactions (6.1, 6.2)].

Electrolyte monitoring:

Inform patients of the need for periodic monitoring of electrolytes [see Warnings and Precautions (5.3)].

Dehydration:

Advise patients of the increased risk of diarrhea and dehydration which may lead to acute renal failure and electrolyte depletion when Vectibix is administered in combination with chemotherapy [see Warnings and Precautions (5.5)].

Infusion reactions:

Advise patients of the risk of infusion reactions [see Dosage and Administration (2.3), Warnings and Precautions (5.4) and Adverse Reactions (6.1, 6.2)].

Respiratory:

Advise patients to contact a healthcare professional if they experience persistent or recurrent coughing, wheezing, dyspnea, or new-onset facial swelling [see Warnings and Precautions (5.6) and Adverse Reactions (6.1)].

Embryo-fetal Toxicity:

Advise pregnant women and females of reproductive potential that Vectibix can result in fetal harm. Advise females of reproductive potential to use effective contraception during treatment with Vectibix, and for at least 2 months after the last dose and to inform their healthcare provider of a known or suspected pregnancy [see Warnings and Precautions (5.10) and Use in Specific Populations (8.1, 8.3)].

Lactation:

Advise women not to breastfeed during treatment with Vectibix and for 2 months after the last dose [see Use in Specific Populations (8.2)].

Infertility:

Advise females of reproductive potential of the potential for reduced fertility from Vectibix [see Use in Specific Populations (8.3)].

Sun exposure:

Advise patients to limit sun exposure (use sunscreen, wear hats) while receiving Vectibix and for 2 months after the last dose of Vectibix therapy [see Warnings and Precautions (5.7)].

Vectibix in Combination with Sotorasib:

Advise patients taking Vectibix in combination with sotorasib:

- to take the first dose of sotorasib prior to the first Vectibix infusion [see Dosage and Administration (2.2)].
- stop taking Vectibix whenever sotorasib is withheld or discontinued [see Dosage and Administration (2.3)].

Vectibix® (panitumumab)
Manufactured by:
Amgen Inc.
One Amgen Center Drive
Thousand Oaks, CA 91320-1799 U.S.A.
U.S. License No. 1080

Patent: http://pat.amgen.com/vectibix/

© 2006-2025 Amgen Inc. All rights reserved.
1xxxxxx – v27

PACKAGE LABEL

PRINCIPAL DISPLAY PANEL

Single-Dose Vial

NDC 55513-954-01

AMGEN®

Vectibix®

(panitumumab)

Injection

100 mg

Each 5 mL single-dose vial of

Vectibix® contains 100 mg

panitumumab in a sterile,

preservative-free solution

(pH 5.8) containing 29 mg sodium

chloride and 34 mg sodium acetate

in Water for Injection, USP.

Store at 2° to 8°C.

Do not freeze or shake.

Protect from direct sunlight.

Rx Only

PACKAGE LABEL

PRINCIPAL DISPLAY PANEL

Single-Dose Vial

NDC55513-956-01

AMGEN®

Vectibix®

(panitumumab)

Injection

400 mg

Each 20 mL single-dose vial

of Vectibix® contains 400 mg

panitumumab in a sterile,

preservative-free solution

(pH 5.8) containing 117 mg

sodium chloride and 136 mg

sodium acetate in Water for

Injection, USP.

Store at 2° to 8°C.

Do not freeze or shake.

Protect from direct sunlight.

Rx Only